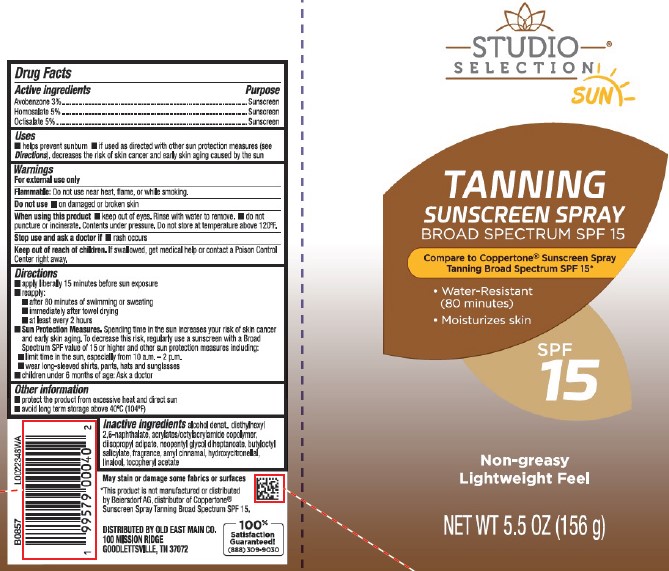 DRUG LABEL: Tanning Sunscreen SPF 15
NDC: 75712-139 | Form: AEROSOL, SPRAY
Manufacturer: Old East Main Co.
Category: otc | Type: HUMAN OTC DRUG LABEL
Date: 20260302

ACTIVE INGREDIENTS: AVOBENZONE 30 mg/1 g; OCTISALATE 50 mg/1 g; HOMOSALATE 50 mg/1 g
INACTIVE INGREDIENTS: NEOPENTYL GLYCOL DIHEPTANOATE; HYDROXYCITRONELLAL; DIETHYLHEXYL 2,6-NAPHTHALATE; DIISOPROPYL ADIPATE; ACRYLATE/ISOBUTYL METHACRYLATE/N-TERT-OCTYLACRYLAMIDE COPOLYMER (40000 MW); ALCOHOL; .ALPHA.-TOCOPHEROL ACETATE; BUTYLOCTYL SALICYLATE; .ALPHA.-AMYLCINNAMALDEHYDE; LINALOOL, (+/-)-

Studio Selection 139.000/139AA Rev 1
Tanning Sunscreen Spray SPF 15

Active Ingredients

Avobenzone 3%
Homosalate 5%

Octisalate 5%

Purpose

Sunscreen

Uses

- helps prevent sunburn
- if used as directed with other sun protection measures (see Directions), decreases the risk of skin cancer and early skin aging caused by the sun

Warnings

For external use only

Flammable: Do not use near heat, flame, or while smoking.

Do not use

- on damaged or broken skin

When using this product

- keep out of eyes. Rinse with water to remove.
- do not puncture or incinerate. Contents under pressure. Do not store at temperature above 120ºF.

Stop use and ask a doctor if

- rash occurs

Keep out of reach of children.

If swallowed, get medical help or contact a Poison Control Center right away.

Directions

- apply liberally 15 minutes before sun exposure
- reapply:
- after 80 minutes of swimming or sweating
- immediately after towel drying
- at least every 2 hours
- Sun Protection Measures. Spending time in the sun increases your risk of skin cancer and early skin aging. To decrease this risk, regularly use a sunscreen with a Broad Spectrum SPF value of 15 or higher and other sun protection measures including:
- limit time in the sun, especially from 10 a.m. – 2 p.m.
- wear long-sleeved shirts, pants, hats and sunglasses
- children under 6 months of age: Ask a doctor

Other information

- protect the product from excessive heat and direct sun
- avoid long term storage above 40ºC (104ºF)

Inactive ingredients

alcohol denat., diethylhexyl 2,6-naphthalate, acrylates/octylacrylamide copolymer, diisopropyl adipate, neopentyl glycol diheptanoate, butyloctyl salicylate, fragrance, amyl cinnamal, hydroxycitronellal, linalool, tocopheryl acetate

Disclaimers

May stain or damage some fabrics or surfaces

*This product is not manufactured or distributed by Beiersdorf AG, distributor of Coppertone® Sunscreen Spray Tanning Broad Spectrum SPF 15.

Adverse Reactions

DISTRIBUTED BY OLD EAST MAIN CO.

100 MISSION RIDGE

GOODLETTSVILLE, TN 37072

100% Satisfaction Guaranteed!

(888) 309-9030

Principal Display Panel

STUDIO SELECTION®

SUN

TANNING

SUNSCREEN SPRAY

BROAD SPECTRUM SPF 15

Compare to Coppertone® Sunscreen Spray Tanning Broad Spectrum SPF 15*

- Water-Resistant (80 minutes)
- Moisturizes skin

SPF 15

Non-greasy

Lightweight Feel

NET WT 5.5 OZ (156 g)